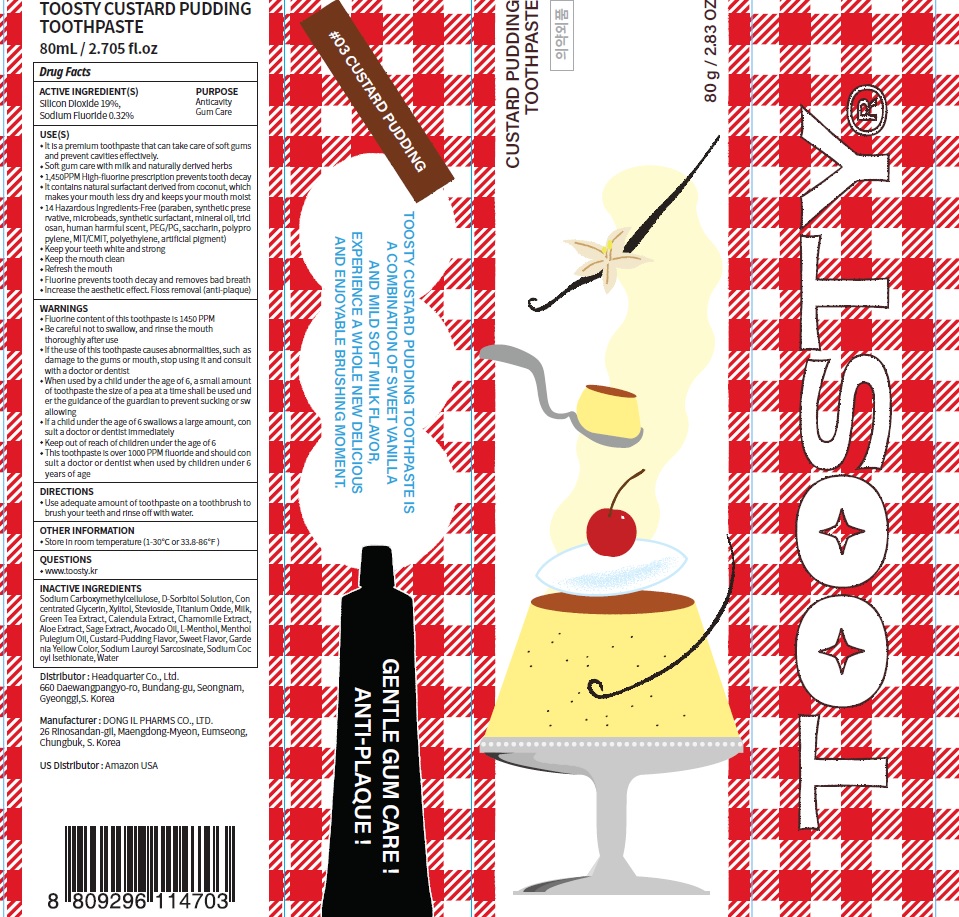 DRUG LABEL: Toosty Custard Pudding Toothpaste
NDC: 82662-030 | Form: PASTE, DENTIFRICE
Manufacturer: Headquarter Co., Ltd
Category: otc | Type: HUMAN OTC DRUG LABEL
Date: 20230726

ACTIVE INGREDIENTS: Silicon Dioxide 19.0 g/100 g; Sodium Fluoride 0.32 g/100 g
INACTIVE INGREDIENTS: CARBOXYMETHYLCELLULOSE SODIUM, UNSPECIFIED; SORBITOL; Glycerin

ACTIVE INGREDIENTS

Silicon Dioxide 19%
Sodium Fluoride 0.32%

INACTIVE INGREDIENTS

Sodium Carboxymethylcellulose, D-Sorbitol Solution, Concentrated Glycerin, Xylitol, Stevioside, Titanium Oxide, Milk, Green Tea Extract, Calendula Extract, Chamomile Extract, Aloe Extract, Sage Extract, Avocado Oil, L-Menthol, Menthol Pulegium Oil, Custard-Pudding Flavor, Sweet Flavor, Gardenia Yellow Color, Sodium Lauroyl Sarcosinate, Sodium Cocoyl Isethionate, Water

PURPOSE

Anticavity
Gum Care

WARNINGS

■ Fluorine content of this toothpaste is 1450 PPM
■ Be careful not to swallow, and rinse the mouth thoroughly after use
■ If the use of this toothpaste causes abnormalities, such as damage to the gums or mouth, stop using it and consult with a doctor or dentist
■ When used by a child under the age of 6, a small amount of toothpaste the size of a pea at a time shall be used under the guidance of the guardian to prevent sucking or swallowing
■ If a child under the age of 6 swallows a large amount, consult a doctor or dentist immediately
■ Keep out of reach of children under the age of 6
■ This toothpaste is over 1000 PPM fluoride and should consult a doctor or dentist when used by children under 6 years of age

Keep out of reach of children under the age of 6

Uses

■ It is a premium toothpaste that can take care of soft gums and prevent cavities effectively.
■ Soft gum care with milk and naturally derived herbs
■ 1,450PPM High-fluorine prescription prevents tooth decay
■ It contains natural surfactant derived from coconut, which makes your mouth less dry and keeps your mouth moist
■ 14 Hazardous Ingredients-Free (paraben, synthetic preservative, microbeads, synthetic surfactant, mineral oil, triclosan, human harmful scent, PEG/PG, saccharin, polypropylene, MIT/CMIT, polyethylene, artificial pigment)
■ Keep your teeth white and strong
■ Keep the mouth clean
■ Refresh the mouth
■ Fluorine prevents tooth decay and removes bad breath
■ Increase the aesthetic effect. Floss removal (anti-plaque)

Directions

■ Use adequate amount of toothpaste on a toothbrush to brush your teeth and rinse off with water.

Other Information

■ Store in room temperature (1-30℃ or 33.8-86℉)

Questions

■ www.toosty.kr